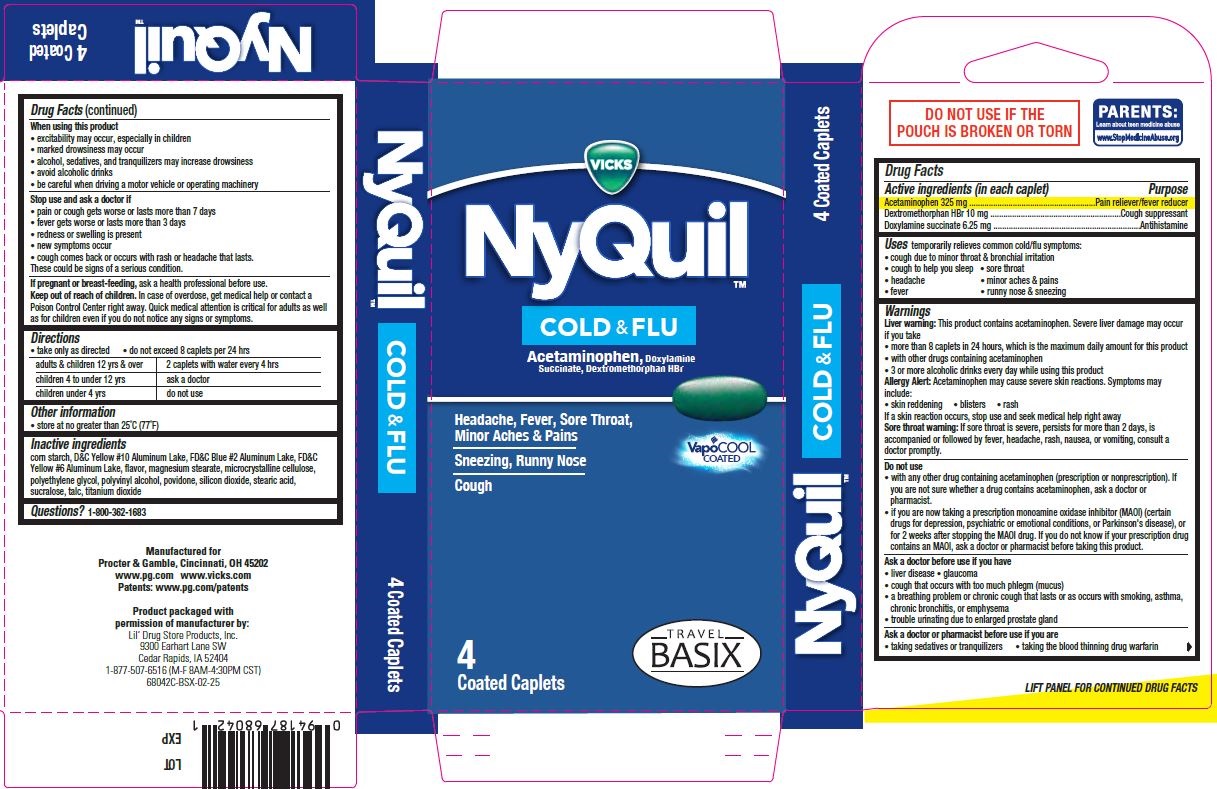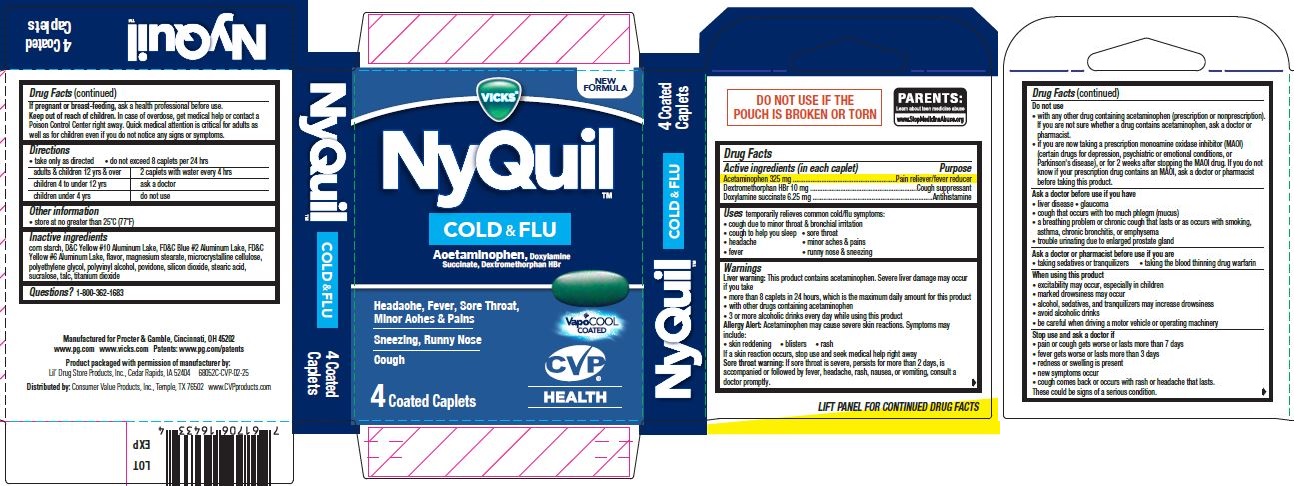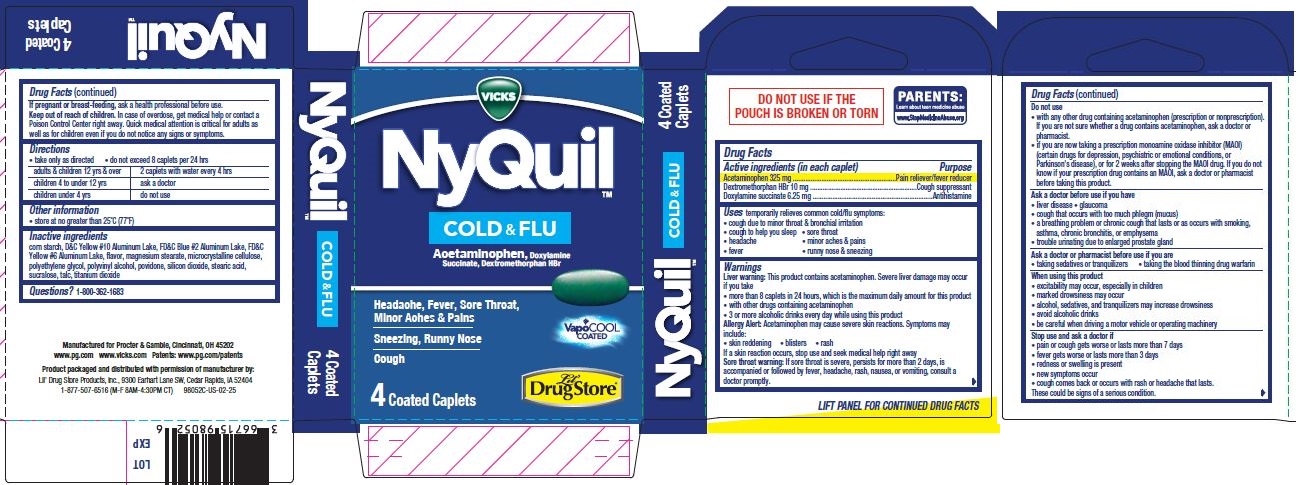 DRUG LABEL: NyQuil Cold and Flu w/VapoCOOL, 4ct, Travel BASIX
NDC: 66715-6205 | Form: TABLET, COATED
Manufacturer: Lil' Drug Store Products, Inc.
Category: otc | Type: HUMAN OTC DRUG LABEL
Date: 20250617

ACTIVE INGREDIENTS: DOXYLAMINE SUCCINATE 6.25 mg/1 1; ACETAMINOPHEN 325 mg/1 1; DEXTROMETHORPHAN HYDROBROMIDE 10 mg/1 1
INACTIVE INGREDIENTS: POVIDONE, UNSPECIFIED; STEARIC ACID; SUCRALOSE; TALC; D&C YELLOW NO. 10 ALUMINUM LAKE; MAGNESIUM STEARATE; POLYVINYL ALCOHOL, UNSPECIFIED; POLYETHYLENE GLYCOL, UNSPECIFIED; FD&C BLUE NO. 2 ALUMINUM LAKE; SILICON DIOXIDE; MICROCRYSTALLINE CELLULOSE; TITANIUM DIOXIDE; STARCH, CORN

NyQuil™ Cold & Flu w/VapoCOOL, 4ct (PE-free), Lil' Drug Store®
NyQuil™ Cold & Flu w/VapoCOOL, 4ct (PE-free), CVP® HEALTH
NyQuil™ Cold & Flu w/VapoCOOL, 4ct (PE-free), Travel BASIX

Active ingredients

Active ingredients (in each caplet)

Acetaminophen 325 mg

Dextromethorphan HBr 10 mg

Doxylamine succinate 6.25 mg

Purpose

Pain reliever/fever red

Cough suppressant

Antihistamine

Uses

temporarily relieves common cold/flu symptoms:

- cough due to minor throat & bronchial irritation
- cough to help you sleep
- sore throat
- headache
- minor aches & pains
- fever
- runny nose & sneezing

Warnings

Liver warning

Liver warning: This product contains acetaminophen. Severe liver damage may occur if you take

- more than 8 caplets in 24 hours, which is the maximum daily amount for this product
- with other drugs containing acetaminophen
- 3 or more alcoholic drinks every day while using this product

Allergy Alert

Allergy Alert: Acetaminophen may cause severe skin reactions. Symptoms may include:

- skin reddening
- blisters
- rash

If a skin reaction occurs, stop use and seek medical help right away

Sore throat warning: If sore throat is severe, persists for more than 2 days, is accompanied or followed by fever, headache, rash, nausea, or vomiting, consult a doctor promptly.

Do not use

• with any other drug containing acetaminophen (prescription or nonprescription). If you are not sure whether a drug contains acetaminophen, ask a doctor or pharmacist.
• if you are now taking a prescription monoamine oxidase inhibitor (MAOI) (certain drugs for depression, psychiatric or emotional conditions, or Parkinson's disease), or for 2 weeks after stopping the MAOI drug. If you do not know if your prescription drug contains an MAOI, ask a doctor or pharmacist before taking this product.

Ask a doctor before use if you have

- liver disease
- glaucoma
- cough that occurs with too much phlegm (mucus)
- a breathing problem or chronic cough that lasts or as occurs with smoking, asthma, chronic bronchitis, or emphysema
- trouble urinating due to enlarged prostate gland

Ask a doctor or pharmacist before use if you are

- taking sedatives or tranquilizers
- taking the blood thinning drug warfarin

When using this product

- excitability may occur, especially in children
- marked drowsiness may occur
- alcohol, sedatives, and tranquilizers may increase drowsiness
- avoid alcoholic drinks
- be careful when driving a motor vehicle or operating machinery

Stop use and ask a doctor if

- pain or cough gets worse or lasts more than 7 days
- fever gets worse or lasts more than 3 days
- redness or swelling is present
- new symptoms occur
- cough comes back or occurs with rash or headache that lasts.

These could be signs of a serious condition.

If pregnant or breast-feeding, ask a health professional before use.

Keep out of reach of children. In case of overdose, get medical help or contact a
Poison Control Center right away. Quick medical attention is critical for adults as
well as for children even if you do not notice any signs or symptoms.

Directions

- take only as directed
- do not exceed 8 caplets per 24 hrs

adults & children 12 yrs & over | 2 caplets with water every 4 hrs
children 4 to under 12 yrs | ask a doctor
children under 4 yrs | do not use

Other information

- store at no greater than 25°C (77°F)

Inactive ingredients

corn starch, D&C Yellow #10 Aluminum Lake, FD&C Blue #2 Aluminum Lake, FD&C Yellow #6 Aluminum Lake, flavor, magnesium stearate, microcrystalline cellulose, polyethylene glycol, polyvinyl alcohol, povidone, silicon dioxide, stearic acid, sucralose, talc, titanium dioxide

Questions?

Questions?1-800-362-1683

NyQuil™ Cold & Flu w/VapoCOOL, 4ct (PE-free), Lil' Drug Store®

VICKS

NyQuil™

COLD & FLU

Acetaminophen, Docylamine

Succinate, Dextromethorphan HBr

[caplet image]

Headache, Fever, Sore Throat,

Minor Aches & Pains

Cough

VapoCOOL

COATED

4 Coated Caplets

[Lil' Drug Store® logo]

NyQuil Cold & Flu w/VapoCOOL, 4ct (PE-free), CVP® HEALTH

VICKS

NyQuil™

COLD & FLU

Acetaminophen, Docylamine

Succinate, Dextromethorphan HBr

[caplet image]

Headache, Fever, Sore Throat,

Minor Aches & Pains

Cough

VapoCOOL

COATED

4 Coated Caplets

[CVP® HEALTH logo]

NyQuil Cold & Flu w/VapoCOOL, 4ct (PE-free), Travel BASIX

VICKS

NyQuil™

COLD & FLU

Acetaminophen, Docylamine

Succinate, Dextromethorphan HBr

[caplet image]

Headache, Fever, Sore Throat,

Minor Aches & Pains

Cough

VapoCOOL

COATED

4 Coated Caplets

[Travel BASIX logo]